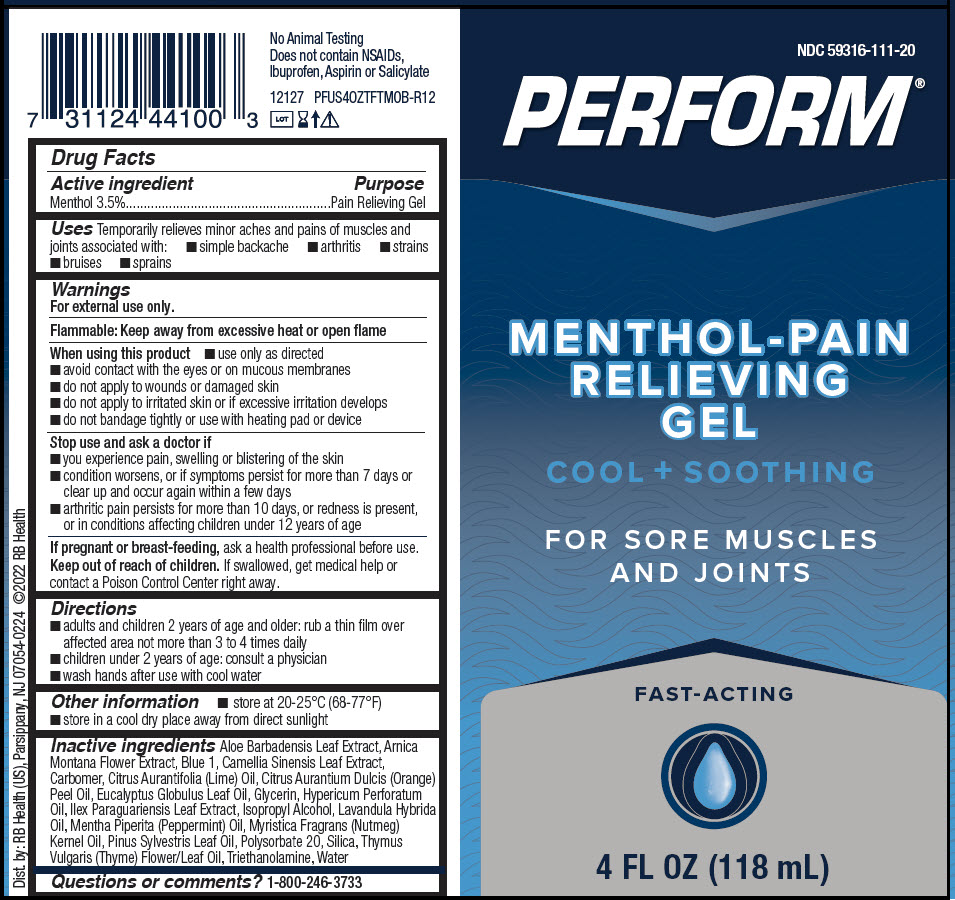 DRUG LABEL: PERFORM COOL and SOOTHING PAIN RELIEVING
NDC: 59316-111 | Form: GEL
Manufacturer: RB Health (US) LLC
Category: otc | Type: HUMAN OTC DRUG LABEL
Date: 20241227

ACTIVE INGREDIENTS: MENTHOL, UNSPECIFIED FORM 35 mg/1 mL
INACTIVE INGREDIENTS: ALOE VERA LEAF; ARNICA MONTANA FLOWER; FD&C BLUE NO. 1; GREEN TEA LEAF; LIME OIL, COLD PRESSED; ORANGE OIL, COLD PRESSED; EUCALYPTUS OIL; GLYCERIN; HYPERICUM OIL; ILEX PARAGUARIENSIS LEAF; ISOPROPYL ALCOHOL; LAVANDIN OIL; PEPPERMINT OIL; NUTMEG OIL; PINE NEEDLE OIL (PINUS SYLVESTRIS); POLYSORBATE 20; SILICON DIOXIDE; THYME OIL; TROLAMINE; WATER

PERFORM®COOL and SOOTHING PAIN RELIEVING

Active ingredient

Menthol 3.5%

Purpose

Pain Relieving Gel

Uses

Temporarily relieves minor aches and pains of muscles and joints associated with:

- simple backache
- arthritis
- strains
- bruises
- sprains

Warnings

For external use only.

Flammable:

Keep away from excessive heat or open flame

When using this product

- use only as directed
- avoid contact with the eyes or on mucous membranes
- do not apply to wounds or damaged skin
- do not apply to irritated skin or if excessive irritation develops
- do not bandage tightly or use with heating pad or device

Stop use and ask a doctor if

- you experience pain, swelling or blistering of the skin
- condition worsens, or if symptoms persist for more than 7 days or clear up and occur again within a few days
- arthritic pain persists for more than 10 days, or redness is present, or in conditions affecting children under 12 years of age

PREGNANCY OR BREAST FEEDING

If pregnant or breast-feeding,ask a health professional before use.

Keep out of reach of children.If swallowed, get medical help or contact a Poison Control Center right away.

Directions

- adults and children 2 years of age and older: rub a thin film over affected area not more than 3 to 4 times daily
- children under 2 years of age: consult a physician
- wash hands after use with cool water

Other information

- store at 20-25°C (68-77°F)
- store in a cool dry place away from direct sunlight

Inactive ingredients

Aloe Barbadensis Leaf Extract, Arnica Montana Flower Extract, Blue 1, Camellia Sinensis Leaf Extract, Carbomer, Citrus Aurantifolia (Lime) Oil, Citrus Aurantium Dulcis (Orange) Peel Oil, Eucalyptus Globulus Leaf Oil, Glycerin, Hypericum Perforatum Oil, Ilex Paraguariensis Leaf Extract, Isopropyl Alcohol, Lavandula Hybrida Oil, Mentha Piperita (Peppermint) Oil, Myristica Fragrans (Nutmeg) Kernel Oil, Pinus Sylvestris Leaf Oil, Polysorbate 20, Silica, Thymus Vulgaris (Thyme) Flower/Leaf Oil, Triethanolamine, Water

Questions or comments?

1-800-246-3733

Dist. by: RB Health (US), Parsippany, NJ 07054-0224

PRINCIPAL DISPLAY PANEL - 118 mL Tube Label

NDC 59316-111-20

PERFORM®

MENTHOL-PAIN
RELIEVING
GEL

COOL + SOOTHING

FOR SORE MUSCLES
AND JOINTS

FAST-ACTING

4 FL OZ (118 mL)